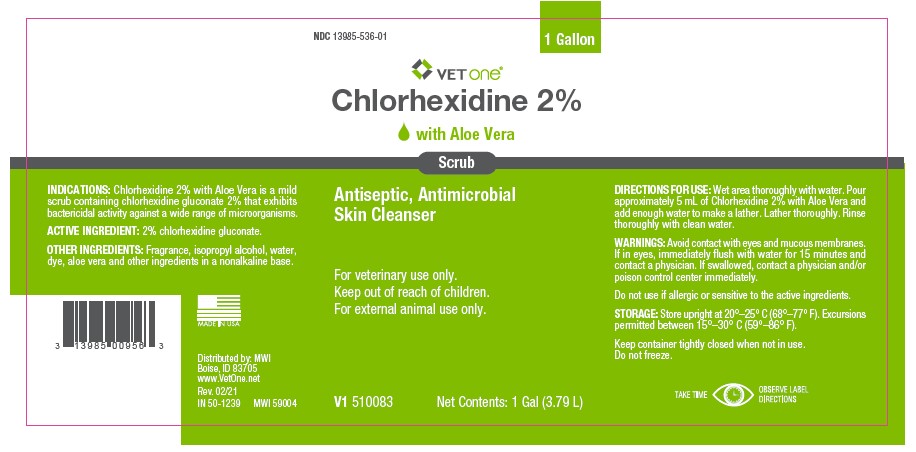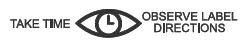 DRUG LABEL: Chlorhexidine
NDC: 13985-536 | Form: SOLUTION
Manufacturer: MWI
Category: animal | Type: OTC ANIMAL DRUG LABEL
Date: 20230224

ACTIVE INGREDIENTS: CHLORHEXIDINE GLUCONATE 20 g/1 L

Chlorhexidine 2% with Aloe Vera Scrub

INDICATIONS:

Chlorhexidine 2% with Aloe Vera is a mild scrub containing chlorhexidine gluconate 2% that exhibits bactericidal activity against a wide range of microorganisms.

ACTIVE INGREDIENTS:

2% chlorhexidine gluconate.

OTHER INGREDIENTS:

Fragrance, isopropyl alcohol, water, dye, aloe vera and other ingredients in a nonalkaline base.

DIRECTIONS FOR USE:

Wet area thoroughly with water. Pour approximately 5 mL of Chlorhexidine 2% with Aloe Vera and add enough water to make a lather. Lather thoroughly. Rinse thoroughly with clean water.

WARNING:

Avoid contact with eyes and mucous membranes. If in eyes, immediately flush with water for 15 minutes and contact a physician. If swallowed, contact a physician and/or poison control center immediately.

Do not use if allergic or sensitive to the active ingredients.

STORAGE:

Store upright at 20°–25° C (68°–77° F). Excursions permitted between 15°–30° C (59°–86° F).

Keep container tightly closed when not in use.

Do not freeze.

IN 50-1239

MWI 59004

Rev. 02/2021

Distributed by: MWI

Boise, ID 83705

www.VetOne.net

MADE IN USA

PRINCIPAL DISPLAY PANEL - 1 Gallon Bottle Label

DC 13985-536-01

1 Gallon

VETone

Chlorhexidine 2%

with Aloe Vera

Scrub

Antiseptic, Antimicrobial

Skin Cleanser

For veterinary use only.

Keep out of reach of children.

For external animal use only.

V1 510083

Net Contents: 1 Gal (3.79 L)